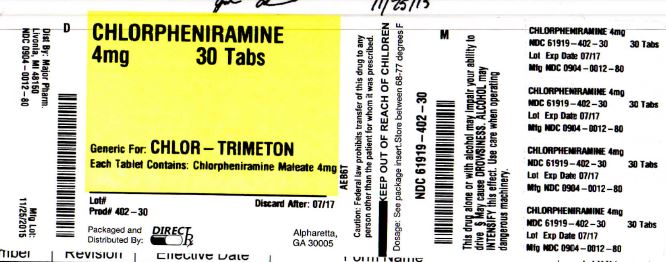 DRUG LABEL: CHLORPHENIRAMINE MALEATE
NDC: 61919-402 | Form: TABLET
Manufacturer: DIRECT RX
Category: otc | Type: HUMAN OTC DRUG LABEL
Date: 20151208

ACTIVE INGREDIENTS: CHLORPHENIRAMINE MALEATE 4 mg/1 1
INACTIVE INGREDIENTS: ANHYDROUS LACTOSE; D&C YELLOW NO. 10; MAGNESIUM STEARATE; CELLULOSE, MICROCRYSTALLINE

CHLORPHENIRAMINE MALEATE

OTC - ACTIVE INGREDIENT SECTION

Chlorpheniramine maleate 4 mg

OTC - PURPOSE SECTION

Antihistamine

INDICATIONS & USAGE SECTION

temporarily relieves these symptoms due to hay fever or other upper respiratory allergies:
runny nose
itchy, watery eyes
sneezing
itching of the nose or throat

OTC - KEEP OUT OF REACH OF CHILDREN SECTION

- Do not use
  to make a child sleepy.
  Ask a doctor before use if you have
  - a breathing problem such as emphysema or chronic bronchitis
  - glaucoma
  - trouble urinating due to an enlarged prostate gland
  Ask a doctor or pharmacist before use if you are
  taking sedatives or tranquilizers.
  When using this product
  - drowsiness may occur
  - avoid alcoholic beverages
  - alcohol, sedatives, and tranquilizers may increase drowsiness
  - use caution when driving a motor vehicle or operating machinery
  - excitability may occur, especially in children
  If pregnant or breast-feeding,
  ask a health professional before use.
  Keep out of reach of children.
  In case of overdose, get medical help or contact a Poison Control Center (1-800-222-1222) right away.

DOSAGE & ADMINISTRATION SECTION

-
  adults and children 12 years of age and over |  | 1 tablet every 4 to 6 hours. Do not take more than 6 tablets in 24 hours.
  children 6 to under 12 years of age |  | 1/2 tablet (break tablet in half) every 4 to 6 hours. Do not exceed 3 whole tablets in 24 hours.
  children under 6 years of age |  | do not use this product in children under 6 years of age

INFORMATION FOR PATIENTS SECTION

- store at 25ºC (77ºF); excursions permitted between 15º-30ºC (59º-86ºF)
- protect from excessive moisture
- see end flap for expiration date and lot number

INACTIVE INGREDIENT SECTION

- corn starch, D&C yellow #10 aluminum lake, lactose anhydrous, magnesium stearate, microcrystalline cellulose

OTC - QUESTIONS SECTION

(800) 616-2471

WARNINGS SECTION

Do not use

to make a child sleepy.

Ask a doctor before use if you have
a breathing problem such as emphysema or chronic bronchitis
glaucoma
trouble urinating due to an enlarged prostate gland

Ask a doctor or pharmacist before use if you are

taking sedatives or tranquilizers.

When using this product
drowsiness may occur
avoid alcoholic beverages
alcohol, sedatives, and tranquilizers may increase drowsiness
use caution when driving a motor vehicle or operating machinery
excitability may occur, especially in children

If pregnant or breast-feeding,

ask a health professional before use.

Keep out of reach of children.

In case of overdose, get medical help or contact a Poison Control Center (1-800-222-1222) right away